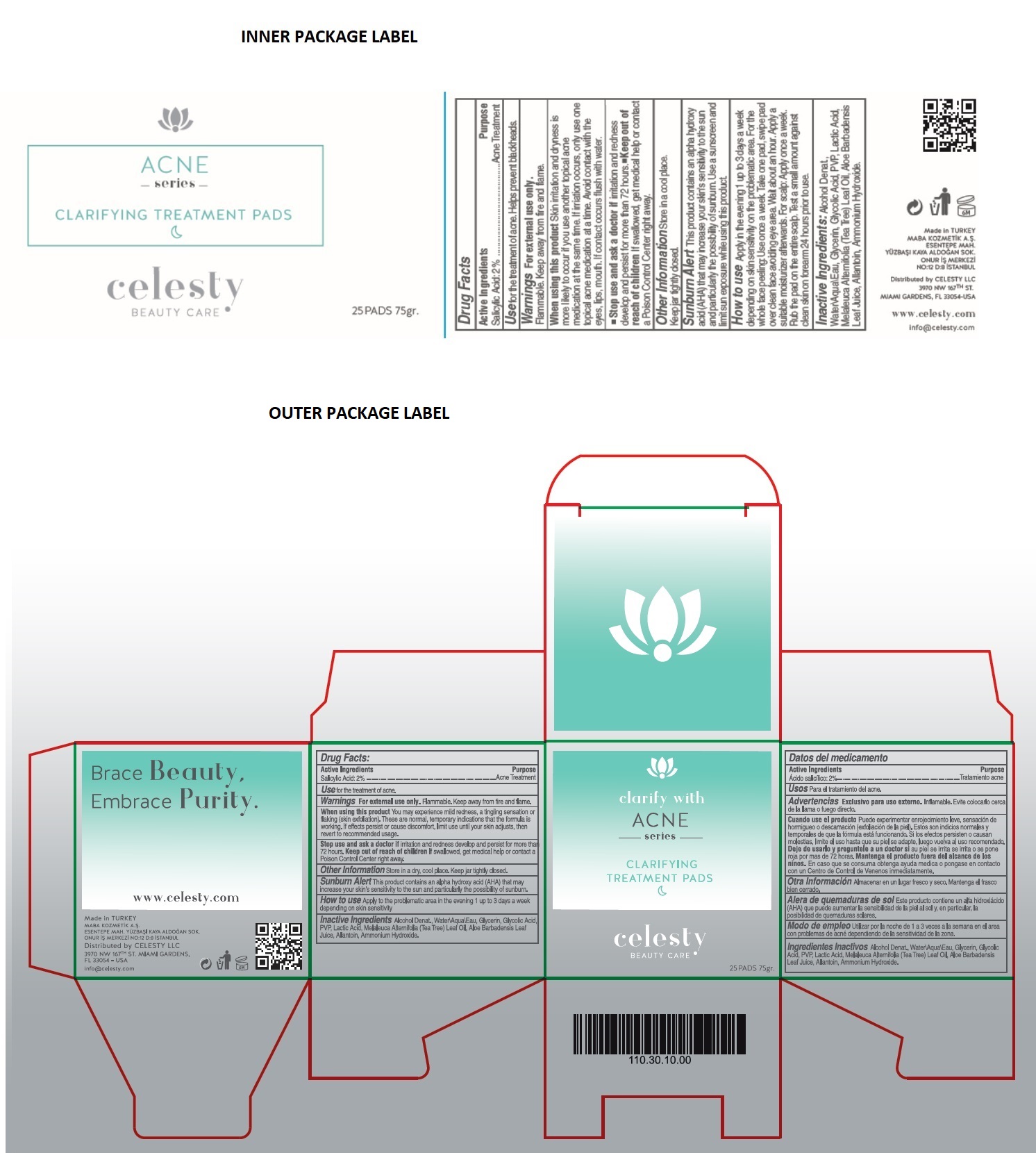 DRUG LABEL: Celesty
NDC: 81120-101 | Form: CLOTH
Manufacturer: MABA KOZMETIK LIMITED SIRKETI
Category: otc | Type: HUMAN OTC DRUG LABEL
Date: 20201209

ACTIVE INGREDIENTS: SALICYLIC ACID 20 mg/1 mL
INACTIVE INGREDIENTS: ALCOHOL; WATER; GLYCERIN; GLYCOLIC ACID; POVIDONE, UNSPECIFIED; LACTIC ACID, UNSPECIFIED FORM; TEA TREE OIL; ALOE VERA LEAF; ALLANTOIN; AMMONIA

Celesty ACNE series CLARIFYING TREATMENT PADS

Active Ingredients

Salicylic Acid: 2%

Purpose

Acne Treatment

Use

for the treatment of acne. Helps prevent blackheads.

Warnings

For external use only. Flammable. Keep away from fire and flame.

When using this product Skin irritation and dryness is more likely to occur if you use another topical acne medication at the same time. If irritation occurs, only use one topical acne medication at a time. Avoid contact with the eyes, lips, mouth. If contact occurs flush with water.

You may experience mild redness, a tingling sensation or flaking (skin exfoliation). These are normal, temporary indications that the formula is working. If effects persist or cause discomfort, limit use until your skin adjusts, then revert to recommended usage.

Stop use and ask a doctor if irritation and redness develop and persist for more than 72 hours.

Keep out of reach of children If swallowed, get medical help or contact a Poison Control Center right away.

How to use

Apply to the problematic area in the evening 1 up to 3 days a week depending on skin sensitivity. For the whole face peeling: Use once a week. Take one pad, swipe pad over clean face avoiding eye area. Wait about an hour. Apply a suitable moisturizer afterwards. For scalp: Apply once a week. Rub the pad on the entire scalp. Test a small amount against clean skin on forearm 24 hours prior to use.

Other Information

Store in a dry, cool place. Keep jar tightly closed.

Sunburn Alert This product contains an alpha hydroxy acid (AHA) that may increase your skin's sensitivity to the sun and particularly the possibility of sunburn. Use a sunscreen and limit sun exposure while using this product.

Inactive Ingredients

Alcohol Denat., Water\Aqua\Eau, Glycerin, Glycolic Acid, PVP, Lactic Acid, Melaleuca Alternifolia (Tea Tree) Leaf Oil, Aloe Barbadensis Leaf Juice, Allantoin, Ammonium Hydroxide.

clarify with ACNE series

BEAUTY CARE

Brace Beauty, Embrace Purity.

www.celesty.com

Made in TURKEY

MABA KOZMETIK A.S.

ESENTEPE MAH. YUZBASI KAYA ALDOGAN SOK.

ONUR IS MERKEZI NO:12 D:8 ISTANBUL

Distributed by CELESTY LLC

3970 NW 167TH ST. MIAMI GARDENS,

FL 33054 -USA

info@celesty.com